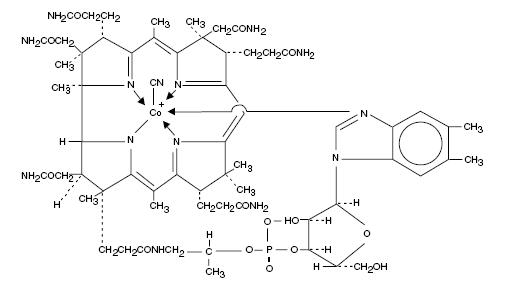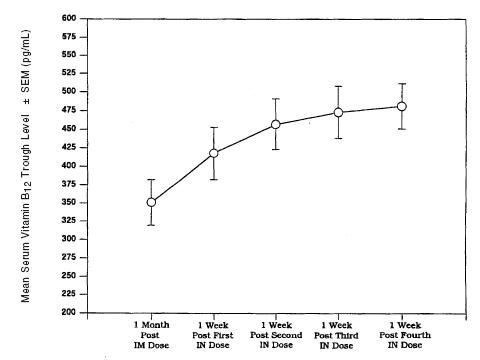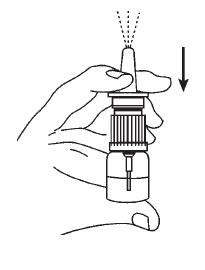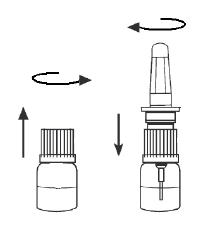 DRUG LABEL: Unknown
Manufacturer: QOL Medical, LLC
Category: prescription | Type: HUMAN PRESCRIPTION DRUG LABELING
Date: 20060915

Nascobal®
Nasal spray
(Cyanocobalamin, USP)
500 mcg/spray
2.3 mL (8 sprays)

DESCRIPTION

Cyanocobalamin is a synthetic form of vitamin B12 with equivalent vitamin B12 activity. The chemical name is 5,6-dimethyl-benzimidazolyl cyanocobamide. The cobalt content is 4.35%. The molecular formula is C63H88CoN14O14P, which corresponds to a molecular weight of 1355.38 and the following structural formula:

Cyanocobalamin occurs as dark red crystals or orthorhombic needles or crystalline red powder. It is very hygroscopic in the anhydrous form, and sparingly to moderately soluble in water (1:80). Its pharmacologic activity is destroyed by heavy metals (iron) and strong oxidizing or reducing agents (vitamin C), but not by autoclaving for short periods of time (15-20 minutes) at 121°C. The vitamin B12 coenzymes are very unstable in light.

Nascobal® Nasal Spray is a solution of Cyanocobalamin, USP (vitamin B12) for administration as a spray to the nasal mucosa. Each bottle of Nascobal Nasal Spray contains 2.3 mL of a 500 mcg / 0.1 mL solution of cyanocobalamin with sodium citrate, citric acid, glycerin and benzalkonium chloride in purified water. The spray solution has a pH between 4.5 and 5.5. The spray pump unit must be fully primed (see DOSAGE AND ADMINISTRATION) prior to initial use. After initial priming, each spray delivers an average of 500 mcg of cyanocobalamin and the 2.3 mL of spray solution contained in the bottle will deliver 8 doses of Nascobal Nasal Spray. The unit must be re-primed before each dose. (See DOSAGE AND ADMINISTRATION.)

CLINICAL PHARMACOLOGY

GENERAL PHARMACOLOGY AND MECHANISM OF ACTION

Vitamin B12 is essential to growth, cell reproduction, hematopoiesis, and nucleoprotein and myelin synthesis. Cells characterized by rapid division (e.g., epithelial cells, bone marrow, myeloid cells) appear to have the greatest requirement for vitamin B12. Vitamin B12 can be converted to coenzyme B12 in tissues, and as such is essential for conversion of methylmalonate to succinate and synthesis of methionine from homocysteine, a reaction which also requires folate. In the absence of coenzyme B12, tetrahydrofolate cannot be regenerated from its inactive storage form, 5-methyltetrahydrofolate, and a functional folate deficiency occurs. Vitamin B12 also may be involved in maintaining sulfhydryl (SH) groups in the reduced form required by many SH-activated enzyme systems. Through these reactions, vitamin B12 is associated with fat and carbohydrate metabolism and protein synthesis. Vitamin B12 deficiency results in megaloblastic anemia, GI lesions, and neurologic damage that begins with an inability to produce myelin and is followed by gradual degeneration of the axon and nerve head.

Cyanocobalamin is the most stable and widely used form of vitamin B12, and has hematopoietic activity apparently identical to that of the antianemia factor in purified liver extract. The information below, describing the clinical pharmacology of cyanocobalamin, has been derived from studies with injectable vitamin B12.

Vitamin B12 is quantitatively and rapidly absorbed from intramuscular and subcutaneous sites of injection. It is bound to plasma proteins and stored in the liver. Vitamin B12 is excreted in the bile and undergoes some enterohepatic recycling. Absorbed vitamin B12 is transported via specific B12 binding proteins, transcobalamin I and II, to the various tissues. The liver is the main organ for vitamin B12 storage.

Parenteral (intramuscular) administration of vitamin B12 completely reverses the megaloblastic anemia and GI symptoms of vitamin B12 deficiency; the degree of improvement in neurologic symptoms depends on the duration and severity of the lesions, although progression of the lesions is immediately arrested.

Gastrointestinal absorption of vitamin B12 depends on the presence of sufficient intrinsic factor and calcium ions. Intrinsic factor deficiency causes pernicious anemia, which may be associated with subacute combined degeneration of the spinal cord. Prompt parenteral administration of vitamin B12 prevents progression of neurologic damage.

The average diet supplies about 4 to 15 mcg/day of vitamin B12 in a protein-bound form that is available for absorption after normal digestion. Vitamin B12 is not present in foods of plant origin, but is abundant in foods of animal origin. In people with normal absorption, deficiencies have been reported only in strict vegetarians who consume no products of animal origin (including no milk products or eggs).

Vitamin B12 is bound to intrinsic factor during transit through the stomach; separation occurs in the terminal ileum in the presence of calcium, and vitamin B12 enters the mucosal cell for absorption. It is then transported by the transcobalamin binding proteins. A small amount (approximately 1% of the total amount ingested) is absorbed by simple diffusion, but this mechanism is adequate only with very large doses. Oral absorption is considered too undependable to rely on in patients with pernicious anemia or other conditions resulting in malabsorption of vitamin B12.

Colchicine, para-aminosalicylic acid, and heavy alcohol intake for longer than 2 weeks may produce malabsorption of vitamin B12.

PHARMACOKINETICS

Absorption

A three way crossover study in 25 fasting healthy subjects was conducted to compare the bioavailability of the B12 nasal spray to the B12 nasal gel and to evaluate the relative bioavailability of the nasal formulations as compared to the intramuscular injection. The peak concentrations after administration of intranasal spray were reached in 1.25 +/- 1.9 hours. The average peak concentration of B12 obtained after baseline correction following administration of intranasal spray was 757.96 +/- 532.17 pg/mL. The bioavailability of the nasal spray relative to the intramuscular injection was found to be 6.1%. The bioavailability of the B12 nasal spray was found to be 10% less than the B12 nasal gel. The 90% confidence intervals for the loge-transformed AUC(0-t) and Cmax was 71.71% - 114.19% and 71.6% - 118.66% respectively.

In pernicious anemia patients, once weekly intranasal dosing with 500 mcg B12 gel resulted in a consistent increase in pre-dose serum B12 levels during one month of treatment (p < 0.003) above that seen one month after 100 mcg intramuscular dose (Figure).

Distribution

In the blood, B12 is bound to transcobalamin II, a specific B-globulin carrier protein, and is distributed and stored primarily in the liver and bone marrow.

Elimination

About 3-8 mcg of B12 is secreted into the GI tract daily via the bile; in normal subjects with sufficient intrinsic factor, all but about 1 mcg is reabsorbed. When B12 is administered in doses which saturate the binding capacity of plasma proteins and the liver, the unbound B12 is rapidly eliminated in the urine. Retention of B12 in the body is dose-dependent. About 80-90% of an intramuscular dose up to 50 mcg is retained in the body; this percentage drops to 55% for a 100 mcg dose, and decreases to 15% when a 1000 mcg dose is given.

Figure. Vitamin B12 Serum Trough Levels After Intramuscular Solution (IM) of 100 mcg and Nasal Gel (IN) Administration of 500 mcg Cyanocobalamin After Weekly Doses.

INDICATIONS AND USAGE

Nascobal Nasal Spray is indicated for the maintenance of normal hematologic status in pernicious anemia patients who are in remission following intramuscular vitamin B12 therapy and who have no nervous system involvement.

Nascobal Nasal Spray is also indicated as a supplement for other vitamin B12 deficiencies, including:

I. Dietary deficiency of vitamin B12 occurring in strict vegetarians (Isolated vitamin B12 deficiency is very rare).

II. Malabsorption of vitamin B12 resulting from structural or functional damage to the stomach, where intrinsic factor is secreted, or to the ileum, where intrinsic factor facilitates vitamin B12 absorption. These conditions include HIV infection, AIDS, Crohn's disease, tropical sprue, and nontropical sprue (idiopathic steatorrhea, gluten-induced enteropathy). Folate deficiency in these patients is usually more severe than vitamin B12 deficiency.

III. Inadequate secretion of intrinsic factor, resulting from lesions that destroy the gastric mucosa (ingestion of corrosives, extensive neoplasia), and a number of conditions associated with a variable degree of gastric atrophy (such as multiple sclerosis, HIV infection, AIDS, certain endocrine disorders, iron deficiency, and subtotal gastrectomy). Total gastrectomy always produces vitamin B12 deficiency. Structural lesions leading to vitamin B12 deficiency include regional ileitis, ileal resections, malignancies, etc.

IV. Competition for vitamin B12 by intestinal parasites or bacteria. The fish tapeworm (Diphyllobothrium latum) absorbs huge quantities of vitamin B12 and infested patients often have associated gastric atrophy. The blind loop syndrome may produce deficiency of vitamin B12 or folate.

V. Inadequate utilization of vitamin B12. This may occur if antimetabolites for the vitamin are employed in the treatment of neoplasia.

It may be possible to treat the underlying disease by surgical correction of anatomic lesions leading to small bowel bacterial overgrowth, expulsion of fish tapeworm, discontinuation of drugs leading to vitamin malabsorption (see Drug/Laboratory Test Interactions), use of a gluten free diet in nontropical sprue, or administration of antibiotics in tropical sprue. Such measures remove the need for long-term administration of vitamin B12.

Requirements of vitamin B12 in excess of normal (due to pregnancy, thyrotoxicosis, hemolytic anemia, hemorrhage, malignancy, hepatic and renal disease) can usually be met with intranasal or oral supplementation.

Nascobal Nasal Spray is not suitable for vitamin B12 absorption test (Schilling Test).

CONTRAINDICATION

Sensitivity to cobalt and/or vitamin B12 or any component of the medication is a contraindication.

WARNINGS

Patients with early Leber's disease (hereditary optic nerve atrophy) who were treated with vitamin B12 suffered severe and swift optic atrophy.

Hypokalemia and sudden death may occur in severe megaloblastic anemia which is treated intensely with vitamin B12. Folic acid is not a substitute for vitamin B12 although it may improve vitamin B12-deficient megaloblastic anemia. Exclusive use of folic acid in treating vitamin B12-deficient megaloblastic anemia could result in progressive and irreversible neurologic damage.

Anaphylactic shock and death have been reported after parenteral vitamin B12 administration. No such reactions have been reported in clinical trials with Nascobal Nasal Spray or Nascobal Nasal Gel.

Blunted or impeded therapeutic response to vitamin B12 may be due to such conditions as infection, uremia, drugs having bone marrow suppressant properties such as chloramphenicol, and concurrent iron or folic acid deficiency.

PRECAUTIONS

1. GENERAL

An intradermal test dose of parenteral vitamin B12 is recommended before Nascobal Nasal Spray is administered to patients suspected of cyanocobalamin sensitivity. Vitamin B12 deficiency that is allowed to progress for longer than three months may produce permanent degenerative lesions of the spinal cord. Doses of folic acid greater than 0.1 mg per day may result in hematologic remission in patients with vitamin B12 deficiency. Neurologic manifestations will not be prevented with folic acid, and if not treated with vitamin B12, irreversible damage will result.

Doses of vitamin B12 exceeding 10 mcg daily may produce hematologic response in patients with folate deficiency. Indiscriminate administration may mask the true diagnosis.

The validity of diagnostic vitamin B12 or folic acid blood assays could be compromised by medications, and this should be considered before relying on such tests for therapy.

Vitamin B12 is not a substitute for folic acid and since it might improve folic acid deficient megaloblastic anemia, indiscriminate use of vitamin B12 could mask the true diagnosis.

Hypokalemia and thrombocytosis could occur upon conversion of severe megaloblastic to normal erythropoiesis with vitamin B12 therapy. Therefore, serum potassium levels and the platelet count should be monitored carefully during therapy.

Vitamin B12 deficiency may suppress the signs of polycythemia vera. Treatment with vitamin B12 may unmask this condition.

If a patient is not properly maintained with Nascobal® Nasal Spray, intramuscular vitamin B12 is necessary for adequate treatment of the patient. No single regimen fits all cases, and the status of the patient observed in follow-up is the final criterion for adequacy of therapy.

The effectiveness of Nascobal Nasal Spray in patients with nasal congestion, allergic rhinitis and upper respiratory infections has not been determined. Therefore, treatment with Nascobal Nasal Spray should be deferred until symptoms have subsided.

2. INFORMATION FOR PATIENTS

Patients with pernicious anemia should be instructed that they will require weekly intranasal administration of Nascobal Nasal Spray for the remainder of their lives. Failure to do so will result in return of the anemia and in development of incapacitating and irreversible damage to the nerves of the spinal cord. Also, patients should be warned about the danger of taking folic acid in place of vitamin B12, because the former may prevent anemia but allow progression of subacute combined degeneration of the spinal cord.

(Hot foods may cause nasal secretions and a resulting loss of medication; therefore, patients should be told to administer Nascobal Nasal Spray at least one hour before or one hour after ingestion of hot foods or liquids.)

A vegetarian diet which contains no animal products (including milk products or eggs) does not supply any vitamin B12. Therefore, patients following such a diet should be advised to take Nascobal Nasal Spray weekly. The need for vitamin B12 is increased by pregnancy and lactation. Deficiency has been recognized in infants of vegetarian mothers who were breast fed, even though the mothers had no symptoms of deficiency at the time.

Because the nasal dosage forms of vitamin B12 have a lower absorption than intramuscular dosage, nasal dosage forms are administered weekly, rather than the monthly intramuscular dosage. As shown in the Figure above, at the end of a month, weekly nasal administration results in significantly higher serum vitamin B12 levels than after intramuscular administration. The patient should also understand the importance of returning for follow-up blood tests every 3 to 6 months to confirm adequacy of the therapy.

Careful instructions on the actuator assembly, removal of the safety clip, priming of the actuator and nasal administration of Nascobal Nasal Spray should be given to the patient. Although instructions for patients are supplied with individual bottles, procedures for use should be demonstrated to each patient.

3. LABORATORY TESTS

Hematocrit, reticulocyte count, vitamin B12, folate and iron levels should be obtained prior to treatment. If folate levels are low, folic acid should also be administered. All hematologic parameters should be normal when beginning treatment with Nascobal® Nasal Spray.

Vitamin B12 blood levels and peripheral blood counts must be monitored initially at one month after the start of treatment with Nascobal® Nasal Spray, and then at intervals of 3 to 6 months.

A decline in the serum levels of B12 after one month of treatment with B12 nasal spray may indicate that the dose may need to be adjusted upward. Patients should be seen one month after each dose adjustment; continued low levels of serum B12 may indicate that the patient is not a candidate for this mode of administration.

Patients with pernicious anemia have about 3 times the incidence of carcinoma of the stomach as in the general population, so appropriate tests for this condition should be carried out when indicated.

4. DRUG/LABORATORY TEST INTERACTIONS

Persons taking most antibiotics, methotrexate or pyrimethamine invalidate folic acid and vitamin B12 diagnostic blood assays.

Colchicine, para-aminosalicylic acid and heavy alcohol intake for longer than 2 weeks may produce malabsorption of vitamin B12.

5. CARCINOGENESIS, MUTAGENESIS, IMPAIRMENT OF FERTILITY

Long-term studies in animals to evaluate carcinogenic potential have not been done. There is no evidence from long-term use in patients with pernicious anemia that vitamin B12 is carcinogenic. Pernicious anemia is associated with an increased incidence of carcinoma of the stomach, but this is believed to be related to the underlying pathology and not to treatment with vitamin B12.

6. PREGNANCY

Pregnancy Category C: Animal reproduction studies have not been conducted with vitamin B12. It is also not known whether vitamin B12 can cause fetal harm when administered to a pregnant woman or can affect reproduction capacity. Adequate and well-controlled studies have not been done in pregnant women. However, vitamin B12 is an essential vitamin and requirements are increased during pregnancy. Amounts of vitamin B12 that are recommended by the Food and Nutrition Board, National Academy of Science - National Research Council for pregnant women should be consumed during pregnancy.

7. NURSING MOTHERS

Vitamin B12 appears in the milk of nursing mothers in concentrations which approximate the mother's vitamin B12 blood level. Amounts of vitamin B12 that are recommended by the Food and Nutrition Board, National Academy of Science-National Research Council for lactating women should be consumed during lactation.

8. PEDIATRIC USE

Intake in pediatric patients should be in the amount recommended by the Food and Nutrition Board, National Academy of Science-National Research Council.

ADVERSE REACTIONS

The incidence of adverse experiences described in the Table below are based on data from a short-term clinical trial in vitamin B12 deficient patients in hematologic remission receiving Nascobal (Cyanocobalamin, USP) Gel for Intranasal Administration (N=24) and intramuscular vitamin B12 (N=25). In the pharmacokinetic study comparing Nascobal Nasal Spray and Nascobal Nasal Gel, the incidence of adverse events was similar.

Table. Adverse Experiences by Body System, Number of Patients and Number of Occurrences by Treatment Following Intramuscular and Intranasal Administration of Cyanocobalamin.
Body System | Adverse Experience | Number of Patients (Occurrences)
Body System | Adverse Experience | Vitamin B12 Nasal Gel, 500 mcg; N=24 | Intramuscular Vitamin B12, 100 mcg; N=25
Body as a Whole | Asthenia | 1 (1) | 4 (4)
Body as a Whole | Back Pain | 0 (0) | 1 (1)
Body as a Whole | Generalized Pain | 0 (0) | 2 (3)
Body as a Whole | Headache | 1 (2) [There may be a possible relationship between these adverse experiences and the study drugs. These adverse experiences could have also been produced by the patient's clinical state or other concomitant therapy.] | 5 (11)
Body as a Whole | Infection [Sore throat, common cold] | 3 (4) | 3 (3)
Cardiovascular System | Peripheral Vascular Disorder | 0 (0) | 1 (1)
Digestive System | Dyspepsia | 0 (0) | 1 (2)
Digestive System | Glossitis | 1 (1) | 0 (0)
Digestive System | Nausea | 1 (1) | 1 (1)
Digestive System | Nausea & Vomiting | 0 (0) | 1 (1)
Digestive System | Vomiting | 0 (0) | 1 (1)
Musculoskeletal System | Arthritis | 0 (0) | 2 (2)
Musculoskeletal System | Myalgia | 0 (0) | 1 (1)
Nervous System | Abnormal Gait | 0 (0) | 1 (1)
Nervous System | Anxiety | 0 (0) | 1 (1)
Nervous System | Dizziness | 0 (0) | 3 (3)
Nervous System | Hypoesthesia | 0 (0) | 1 (1)
Nervous System | Incoordination | 0 (0) | 1 (2)
Nervous System | Nervousness | 0 (0) | 1 (3)
Nervous System | Paresthesia | 1 (1) | 1 (1)
Respiratory System | Dyspnea | 0 (0) | 1 (1)
Respiratory System | Rhinitis | 1 (1) | 2 (2)

The intensity of the reported adverse experiences following the administration of Nascobal (Cyanocobalamin, USP) Gel for Intranasal Administration and intramuscular vitamin B12 were generally mild. One patient reported severe headache following intramuscular dosing. Similarly, a few adverse experiences of moderate intensity were reported following intramuscular dosing (two headaches and rhinitis; one dyspepsia, arthritis, and dizziness), and dosing with Nascobal (Cyanocobalamin, USP) Gel for Intranasal Administration (one headache, infection, and paresthesia).

The majority of the reported adverse experiences following dosing with Nascobal (Cyanocobalamin, USP) Gel for Intranasal Administration and intramuscular vitamin B12 were judged to be intercurrent events. For the other reported adverse experiences, the relationship to study drug was judged as "possible" or "remote". Of the adverse experiences judged to be of "possible" relationship to the study drug, anxiety, incoordination, and nervousness were reported following intramuscular vitamin B12 and headache, nausea, and rhinitis were reported following dosing with Nascobal (Cyanocobalamin, USP) Gel for Intranasal Administration.

The following adverse reactions have been reported with parenteral vitamin B12:

Generalized: Anaphylactic shock and death (see WARNINGS and PRECAUTIONS).

Cardiovascular: Pulmonary edema and congestive heart failure early in treatment; peripheral vascular thrombosis.

Hematological: Polycythemia vera.

Gastrointestinal: Mild transient diarrhea.

Dermatological: Itching; transitory exanthema.

Miscellaneous: Feeling of swelling of the entire body.

OVERDOSAGE

No overdosage has been reported with Nascobal Nasal Spray, Nascobal (Cyanocobalamin, USP) Gel for Intranasal Administration or parenteral vitamin B12.

DOSAGE AND ADMINISTRATION

The recommended initial dose of Nascobal Nasal Spray is one spray (500 mcg) administered in ONE nostril once weekly. Nascobal Nasal Spray should be administered at least one hour before or one hour after ingestion of hot foods or liquids. Periodic monitoring of serum B12 levels should be obtained to establish adequacy of therapy.

Before the first dose and administration, the pump must be primed. Remove the clear plastic cover and the plastic safety clip from the pump. To prime the pump, place nozzle between the first and second finger with the thumb on the bottom of the bottle. Pump the unit firmly and quickly until the first appearance of spray. Then prime the pump an additional 2 times. Now the nasal spray is ready for use. The unit must be re-primed before each dose. Prime the pump once immediately before each administration of doses 2 through 8.

See LABORATORY TESTS for monitoring B12 levels and adjustment of dosage.

HOW SUPPLIED

Nascobal Nasal Spray is available as a spray in 3 mL glass bottles containing 2.3 mL of solution. It is available in a dosage strength of 500 mcg per actuation (0.1 mL/actuation). A screw-on actuator is provided. This actuator, following priming, will deliver 0.1 mL of the spray. Nascobal Nasal Spray is provided in a carton containing a nasal spray actuator with dust cover, a bottle of nasal spray solution, and a package insert. One bottle will deliver 8 doses (NDC 67871-773-35).

PHARMACIST ASSEMBLY INSTRUCTIONS FOR NASCOBAL NASAL SPRAY

The pharmacist should assemble the Nascobal Nasal Spray unit prior to dispensing to the patient, according to the following instructions:

1. Open the carton and remove the spray actuator and spray solution bottle.
2. Assemble Nascobal Nasal Spray by first unscrewing the white cap from the spray solution bottle and screwing the actuator unit tightly onto the bottle. Make sure the clear dust cover is on the pump unit.
3. Return the Nascobal Nasal Spray bottle to the carton for dispensing to the patient.

INFORMATION FOR PATIENTS

Patients with pernicious anemia should be instructed that they will require weekly intranasal administration of Nascobal Nasal Spray for the remainder of their lives. Failure to do so will result in return of the anemia and in development of incapacitating and irreversible damage to the nerves of the spinal cord. Also, patients should be warned about the danger of taking folic acid in place of vitamin B12, because the former may prevent anemia but allow progression of subacute combined degeneration of the spinal cord.

(Hot foods may cause nasal secretions and a resulting loss of medication; therefore, patients should be told to administer Nascobal Nasal Spray at least one hour before or one hour after ingestion of hot foods or liquids.)

A vegetarian diet which contains no animal products (including milk products or eggs) does not supply any vitamin B12. Therefore, patients following such a diet should be advised to take Nascobal Nasal Spray weekly. The need for vitamin B12 is increased by pregnancy and lactation. Deficiency has been recognized in infants of vegetarian mothers who were breast fed, even though the mothers had no symptoms of deficiency at the time.

Because the nasal dosage forms of Vitamin B12 have a lower absorption than intramuscular dosage, nasal dosage forms are administered weekly, rather than the monthly intramuscular dosage. As shown in the Figure above, at the end of a month, weekly nasal administration results in significantly higher serum Vitamin B12 levels than after intramuscular administration. The patient should also understand the importance of returning for follow-up blood tests every 3 to 6 months to confirm adequacy of the therapy.

Careful instructions on the actuator assembly, removal of safety clip, priming of the actuator and nasal administration of Nascobal Nasal Spray should be given to the patient. Although instructions for patients are supplied with individual bottles, procedures for use should be demonstrated to each patient.

STORAGE CONDITIONS

Protect from light. Keep covered in carton until ready to use. Store upright at controlled room temperature 15°C to 30°C (59°F to 86°F). Protect from freezing.

Mfd. for QOL Medical, LLC

Kirland, WA 98033, USA

1.866.469.3773

www.nascobal.com

3078

Rev. 02/06-05/06